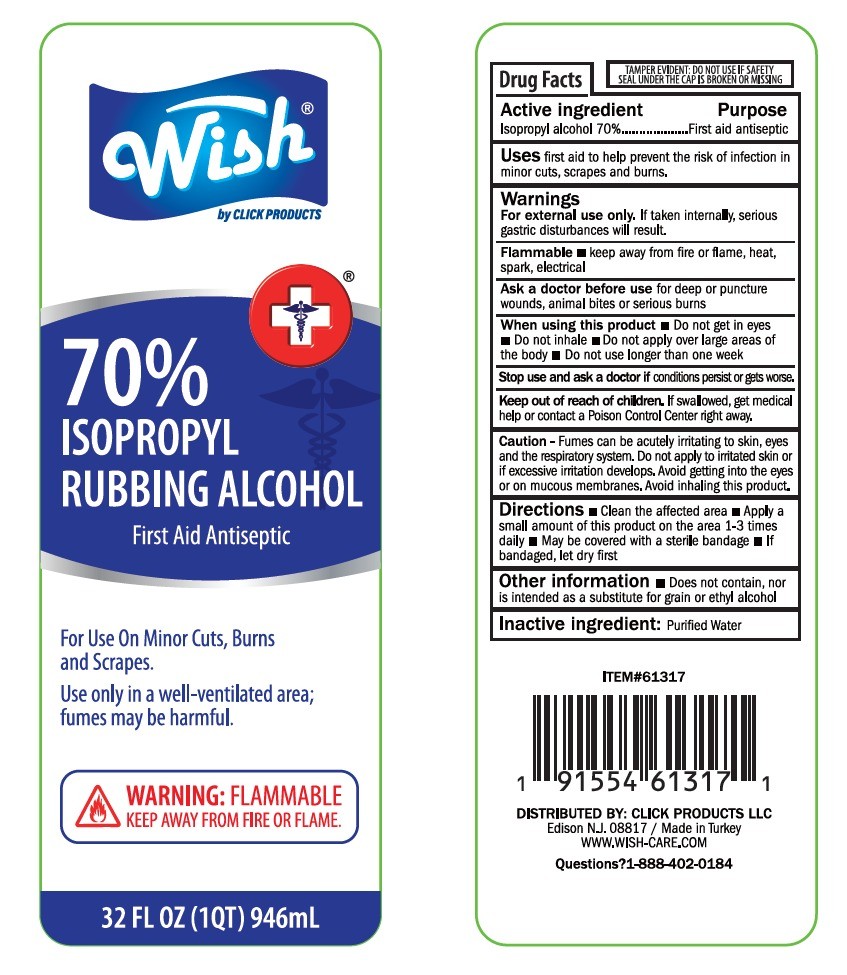 DRUG LABEL: WISH RUBBING ALCOHOL 32oz
NDC: 71611-082 | Form: LIQUID
Manufacturer: CLICK PRODUCTS LLC
Category: otc | Type: HUMAN OTC DRUG LABEL
Date: 20260113

ACTIVE INGREDIENTS: ISOPROPYL ALCOHOL 662.2 mL/946 mL
INACTIVE INGREDIENTS: WATER 283.8 mL/946 mL

Directions

Clean the affected area

Apply a small amount of this product on the area 1-3 times daily

May be covered with a sterile bandage

If bandaged, let dry first

WARNINGS

For external use only.

If taken internally, serious gastrick disturbances will result

Flammable

Keep away from fire or flame, heat, spark, electrical

Ask a doctor before use

for deep or puncture wounds, animal bites or serious burns

INACTIVE INGREDITENT

Purified water

USES

First aid to help prevent the risk of infection in minor cuts, scrapes and burns

KEEP OUT OF REACH OF CHILDREN

If swallowed, get medical help or contact a Poison Control Center right away

PURPOSE

First aid antiseptic

Active Ingredient

Isopropyl alcohol 70%

Purpose

First Aid antiseptic

Uses

First aid to help prevent the risk of infection in minor cuts, scrapes and burns

Warnings

For external use only.

If taken internally, serious gastrick disturbances will result

Flammable

Keep away from fire or flame, heat, spark, electrical

Ask a doctor before use

for deep or puncture wounds, animal bites or serious burns

When using this product

Do not get in eyes

Do not inhale

Do not apply over large areas of the body

Do not use longer than one week

Stop use and ask a doctor if conditionas persist or gets worse

Keep out of reach of children

If swallowed, get medical help or contact a Poison Control Center right away

Caution

Fumes can be acutely irritating to skin, eyes and the respiratory system. Do not apply to irritated skin or if excessive irritation develops. Avoid getting into the yes or on mucous membranes. Avoid inhaling this product.

Directions

Clean the affected area

Apply a small amount of this product on the area 1-3 times daily

May be covered with a sterile bandage

If bandaged, let dry first

Other information Does not container, nor is intended as a substitute for grain or ethyl alcohol

Inactive ingredient

Purified water